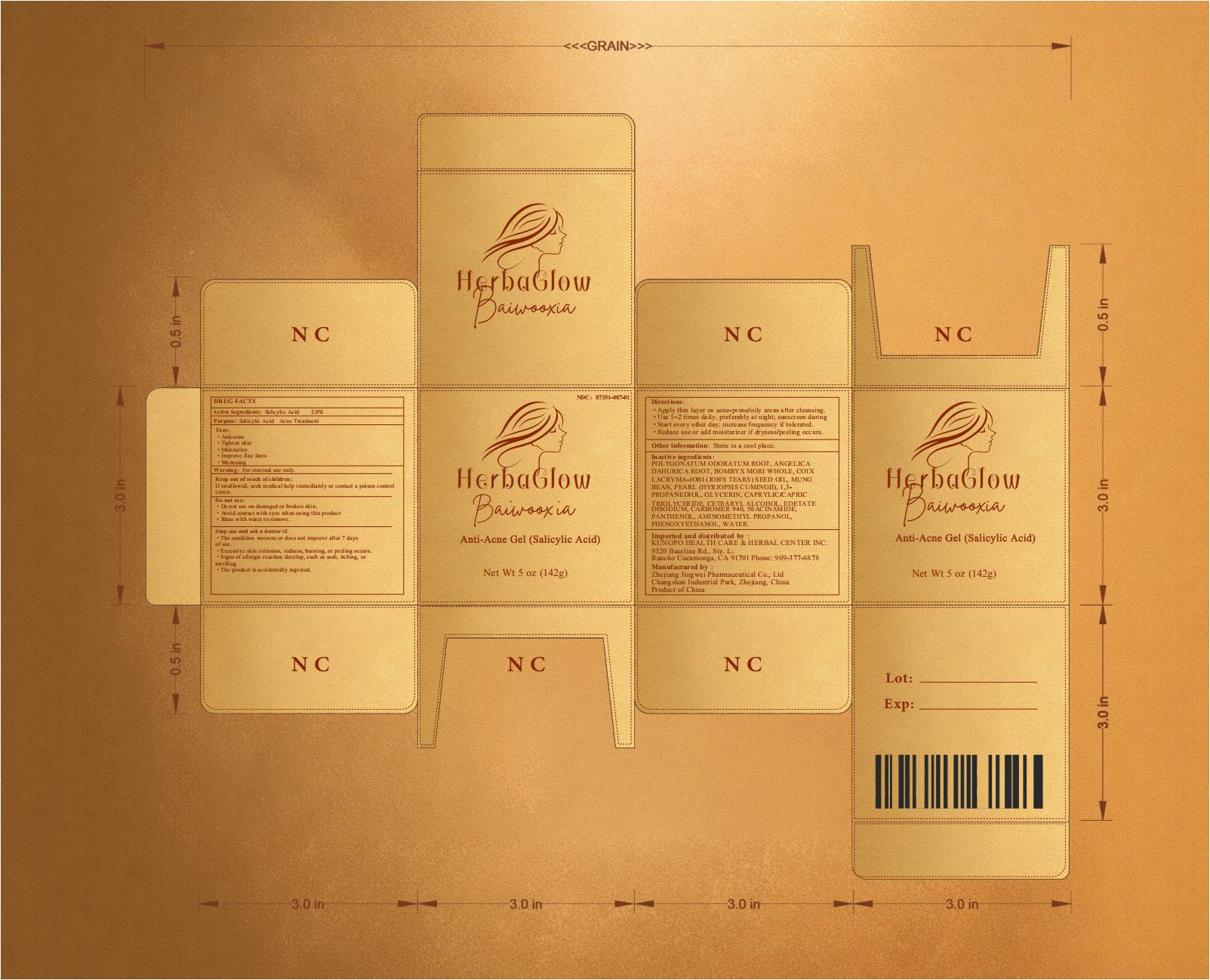 DRUG LABEL: HerbaGlow Baiwooxia Anti-Acne Gel
NDC: 87351-087 | Form: GEL
Manufacturer: Kungpo Health Care & Herbal Center Inc
Category: otc | Type: HUMAN OTC DRUG LABEL
Date: 20260210

ACTIVE INGREDIENTS: SALICYLIC ACID 2 g/100 g
INACTIVE INGREDIENTS: POLYGONATUM ODORATUM ROOT; ANGELICA DAHURICA ROOT; BOMBYX MORI WHOLE; COIX LACRYMA-JOBI (JOB'S TEARS) SEED OIL; MUNG BEAN; PEARL (HYRIOPSIS CUMINGII); 1,3-PROPANEDIOL, 2-(2-(2-AMINO-7H-PURIN-7-YL)ETHYL)-, 1,3-DIACETATE; GLYCERIN; CAPRYLIC/CAPRIC TRIGLYCERIDE; CETEARYL ALCOHOL; EDETATE DISODIUM; CARBOMER 940; NIACINAMIDE; PANTHENOL; AMINOMETHYL PROPANOL; PHENOXYETHANOL; WATER

Active ingredients

Salicylic Acid 2.0%

Purpose

Salicylic Acid Acne Treatment

Uses

- Anti-acne
- Tighten skin
- Moisturize
- Improve fine lines
- Whitening

Warning

For external use only.

- Do not use on damaged or broken skin.
- Avoid contact with eyes when using this product.
- Rinse with water to remove.

Stop use and ask a doctor if

• The condition worsens or does not improve after 7 days of use.
• Excessive skin irritation, redness, burning, or peeling occurs.
• Signs of allergic reaction develop, such as rash, itching, or swelling.
• The product is accidentally ingested.

Keep out of reach of children.

If swallowed, seek medical help immediately or contact a poison control center.

Directions

- Apply thin layer on acne-prone/oily areas after cleansing.
- Use 1–2 times daily, preferably at night; sunscreen during day.
- Start every other day; increase frequency if tolerated.
- Reduce use or add moisturizer if dryness/peeling occurs.

Other information

- Store in a cool place.

Inactive ingredients

POLYGONATUM ODORATUM ROOT, ANGELICA DAHURICA ROOT, BOMBYX MORI WHOLE, COIX LACRYMA-JOBI (JOB'S TEARS) SEED OIL, MUNG BEAN, PEARL (HYRIOPSIS CUMINGII), 1,3-PROPANEDIOL, GLYCERIN, CAPRYLIC/CAPRIC TRIGLYCERIDE, CETEARYL ALCOHOL, EDETATE DISODIUM, CARBOMER 940, NIACINAMIDE, PANTHENOL, AMINOMETHYL PROPANOL, PHENOXYETHANOL, WATER,

Manufactured by

Zhejiang Jingwei Pharmaceutical Co., Ltd
Changshan Industrial Park, Zhejiang, China
Product of China

Imported and distributed by

KUNGPO HEALTH CARE & HERBAL CENTER INC.
9320 Baseline Rd., Ste. L，
Rancho Cucamonga, CA 91701
Phone: 909-377-6878